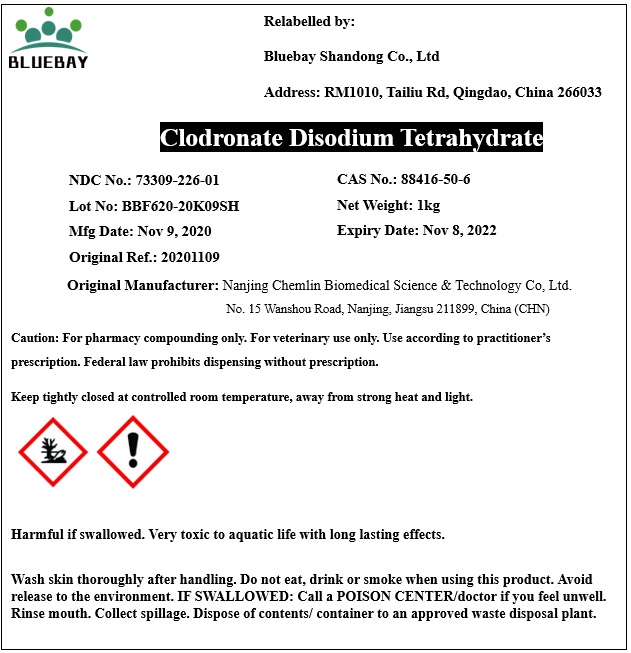 DRUG LABEL: Clodronate Disodium Tetrahydrate
NDC: 73309-226 | Form: POWDER
Manufacturer: BLUEBAY SHANDONG CO.,LTD
Category: other | Type: BULK INGREDIENT
Date: 20220111

ACTIVE INGREDIENTS: Clodronate Disodium 1 kg/1 kg

Clodronate Disodium Tetrahydrate